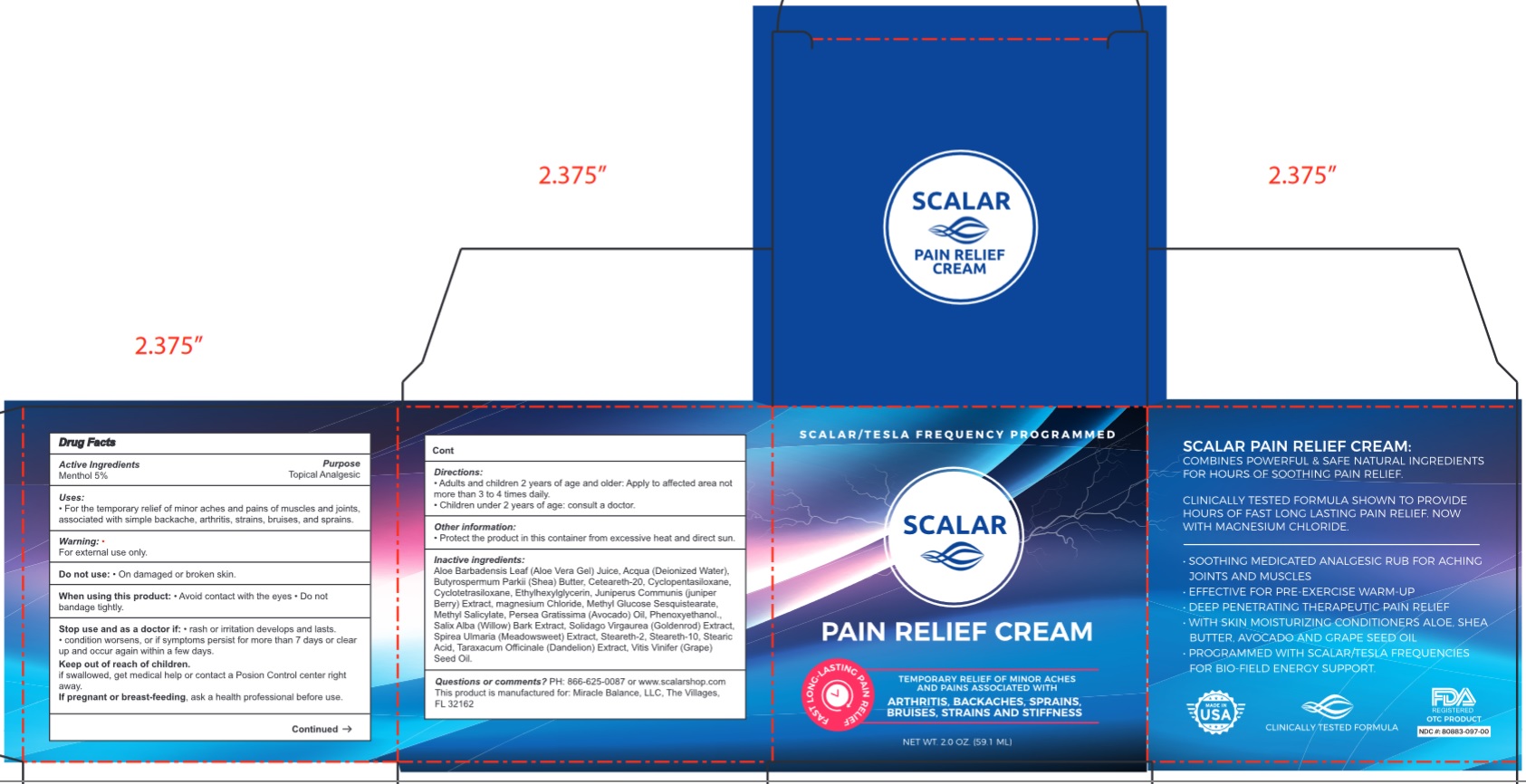 DRUG LABEL: SCALAR Pain Relief Cream
NDC: 80883-097 | Form: CREAM
Manufacturer: Miracle Balance, LLC
Category: otc | Type: HUMAN OTC DRUG LABEL
Date: 20231106

ACTIVE INGREDIENTS: MENTHOL 50 mg/1 mL
INACTIVE INGREDIENTS: ALOE VERA LEAF; WATER; SHEA BUTTER; POLYOXYL 20 CETOSTEARYL ETHER; CYCLOMETHICONE 5; CYCLOMETHICONE 4; ETHYLHEXYLGLYCERIN; JUNIPER BERRY; MAGNESIUM CHLORIDE; METHYL GLUCOSE SESQUISTEARATE; METHYL SALICYLATE; AVOCADO OIL; PHENOXYETHANOL; SALIX ALBA BARK; STEARETH-2; STEARETH-10; STEARIC ACID; TARAXACUM OFFICINALE; GRAPE SEED OIL

SCALAR Pain Relief Cream

Active Ingredients

Menthol 5%

Purpose

Topical Analgesic

Uses:

For the temporary relief of minor aches and pains of muscles and joints, associated with simple backache, arthritis, strains, bruises, and sprains.

Warning:

For external use only

Do not use:

- On damaged or broken skin

When using this product:

- Avoid contact with the eyes
- Do not bandage tightly

Stop use and as a doctor if:

- rash or irritation develops and lasts.
- condition worsens, or if symptoms persist for more than 7 days or clear up and occur again within a few days.

Keep out of reach of children.

if swallowed, get medical help or contact a Poison Control center right away.

If pregnant or breast-feeding,

ask a health professional before use

Directions:

- Adults and children 2 years of age and older: Apply to affected area not more than 3 to 4 times daily.
- Children under 2 years of age: consult a doctor.

Other Information:

- Protect the product in this container from excessive heat and direct sun.

Inactive ingredients:

Aloe Barbadensis Leaf (Aloe Vera Gel) Juice, Aqua (Deionized Water), Butyrospermum Parkii (Shea) Butter, Ceteareth-20, Cyclopentasiloxane, Cyclotetrasiloxane, Ethylhexylglycerin, Juniperus Communis (Juniper Berry) Extract, magnesium Chloride, Methyl Glucose Sesquistearate, Methyl Salicylate, Persea Gratissima (Avocado) Oil, Phenoxyethanol, Salix Alba (Willow) Bark Extract, Solidago Virgaurea (Goldenrod) Extract, Spiraea Ulmaria (Meadowsweet) Extract, Steareth-2, Steareth-10, Stearic Acid, Taraxacum Officinale (Dandelion) Extract, Vitis Vinifera (Grape) Seed Oil.

Questions or comments?

PH: 806-625-0087 or www.scalarshop.com This product is manufacetured for: Miracle Balance, LLC, Delray Beach FL 33483